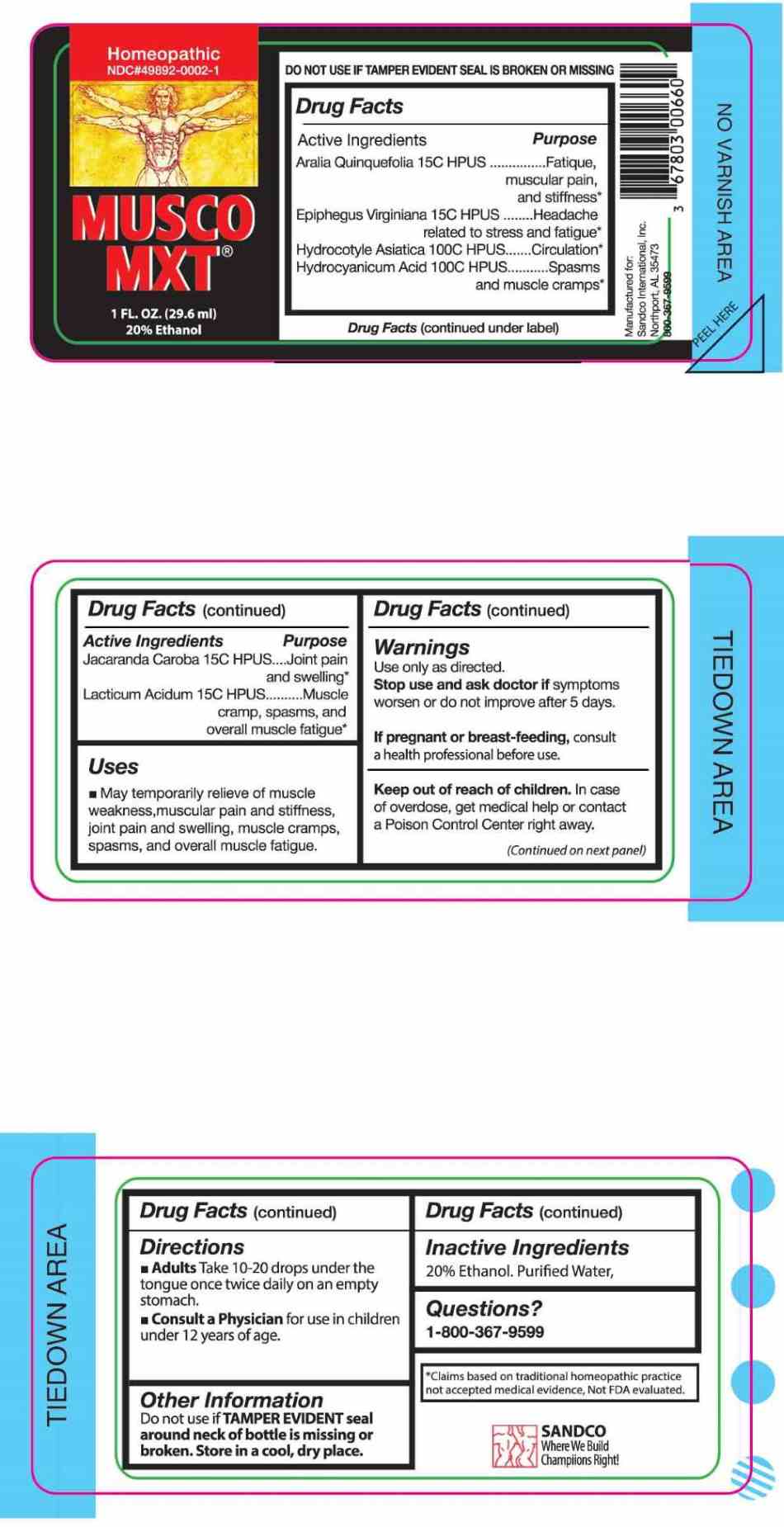 DRUG LABEL: Musco MXT
NDC: 49892-0002 | Form: LIQUID
Manufacturer: Sandco International, Inc
Category: homeopathic | Type: HUMAN OTC DRUG LABEL
Date: 20250408

ACTIVE INGREDIENTS: PANAX QUINQUEFOLIUS WHOLE 15 [hp_C]/1 mL; EPIFAGUS VIRGINIANA WHOLE 15 [hp_C]/1 mL; JACARANDA CAROBA FLOWER 15 [hp_C]/1 mL; LACTIC ACID, DL- 15 [hp_C]/1 mL; CENTELLA ASIATICA WHOLE 100 [hp_C]/1 mL; HYDROGEN CYANIDE 100 [hp_C]/1 mL
INACTIVE INGREDIENTS: WATER; ALCOHOL

DRUG FACTS:

ACTIVE INGREDIENTS:

Aralia Quinquefolia 15C HPUS, Epiphegus Virginiana 15C HPUS, Hydrocotyle Asiatica 100C HPUS, Hydrocyanicum Acidum 100C HPUS, Jacaranda Caroba 15C HPUS, Lacticum Acidum 15C HPUS.

PURPOSE:

Aralia Quinquefolia – Fatigue, muscular pain, and stiffness,* Epiphegus Virginiana – Headache related to stress and fatigue,* Hydrocotyle Asiatica - Circulation,* Hydrocyanicum Acidum – Spasms and muscle cramps,* Jacaranda Caroba – Joint pain and swelling,* Lacticum Acidum – Muscle cramp, spasms, and overall muscle fatigue*
*Claims based on traditional homeopathic practice not accepted medical evidence. Not FDA evaluated.

USES:

- May temporarily relieve of muscle weakness, muscular pain and stiffness, joint pain and swelling, muscle cramps, spasms, and overall muscle fatigue.

WARNINGS:

Use only as directed.

Stop use and ask doctor if symptoms worsen or do not improve after 5 days.

If pregnant or breast-feeding, consult a health professional before use.

Keep out of reach of children. In case of overdose, get medical help or contact a Poison Control Center right away.

Do not use if TAMPER EVIDENT seal around neck of bottle is missing or broken. Store in a cool, dry area.

KEEP OUT OF REACH OR CHILDREN:

In case of overdose, get medical help or contact a Poison Control Center right away.

DIRECTIONS:

- Adults Take 10-20 drops under the tongue once twice daily on an empty stomach.
- Consult a Physician for use in children under 12 years of age.

INACTIVE INGREDIENTS:

20% Ethanol, Purified Water.

QUESTIONS:

Manufactured for:

SANDCO International, Inc.

Northport, AL 35473

1-800-367-9599

PACKAGE LABEL DISPLAY:

Homeopathic

NDC#49892-0002-1

MUSCO MXT

1 FL. OZ (29.6 ml)